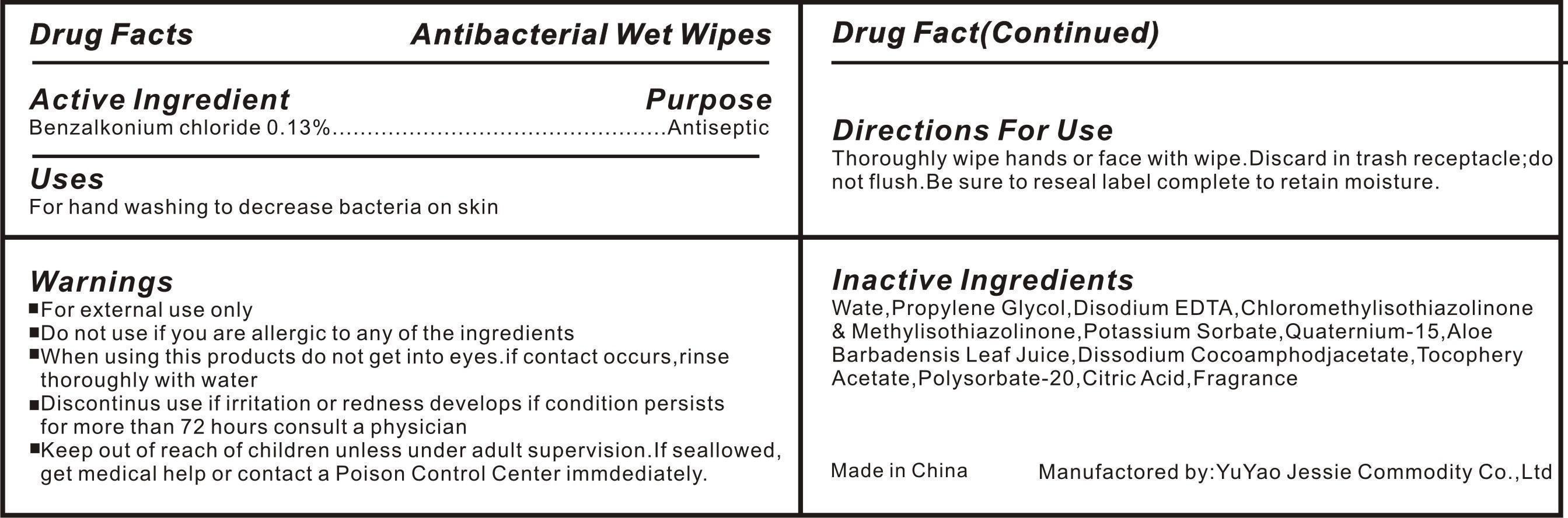 DRUG LABEL: mouth fresh
NDC: 51414-500 | Form: SPRAY
Manufacturer: Yuyao Jessie Commodity Co.,Ltd.
Category: otc | Type: HUMAN OTC DRUG LABEL
Date: 20120912

ACTIVE INGREDIENTS: CETYLPYRIDINIUM CHLORIDE 0.05 mL/100 mL
INACTIVE INGREDIENTS: WATER; PROPYLENE GLYCOL; DISODIUM EDTA-COPPER; CHLOROMETHYL METHYL ETHER; POTASSIUM SORBATE; QUATERNIUM-15; DISODIUM COCOAMPHODIACETATE; ALPHA-TOCOPHEROL ACETATE; POLYSORBATE 20; CITRIC ACID ACETATE

Antibacterial Wet Wipes

Active Ingredient

Cetylpyridinium Chloride 0.05%

Purpose

Sterilization

Use

sterilization

WARNINGS

For External use only.
Do not use if you are allergic to any of the ingredients.
When using this product Do not get into eyes,if contact occurs ,rinse throughly with water.
Discontinue use if irritation or redness develops if condition persists for more than 72 hours consults a physician.

keep out of reach of children unless under adult supervision .if seallowed ,get medical help or contact a Poison Control Center immediately.

Directions

Open Cap to on position exposing nozzle Pump 1-2 sprays directly into mouth.

Children under 6 months of age:ask a doctor

Inactive ingredients

WATER (Aqua),Alcohol,Glycerin,Sorbitol,Aroma,PEG-40 hydrogenated Castor Oil,Sodium Benzoate,Citric Acid ,Limonene